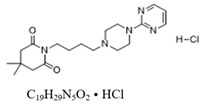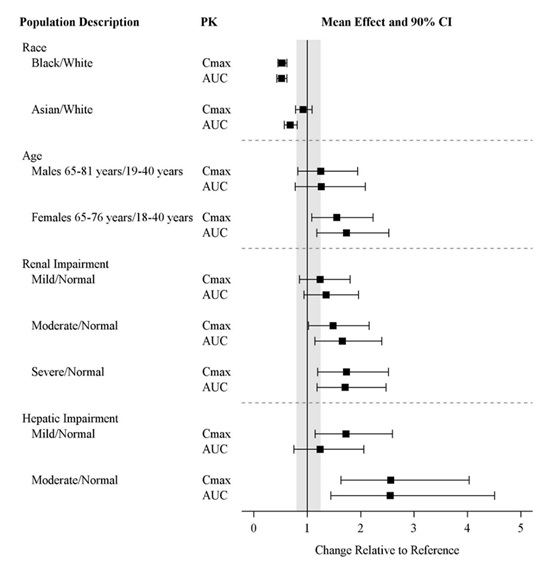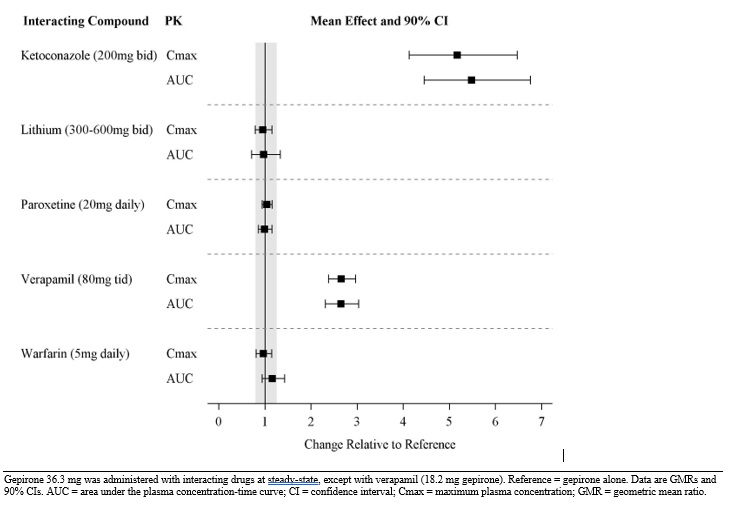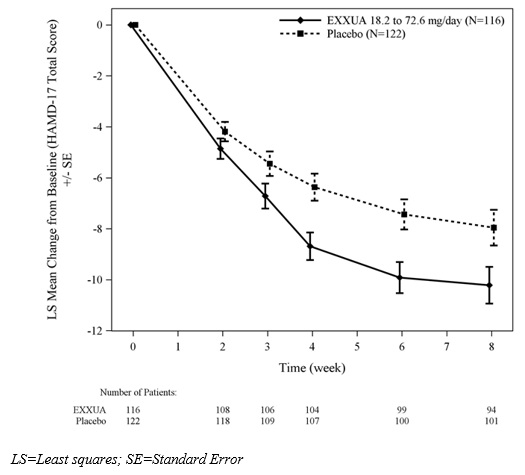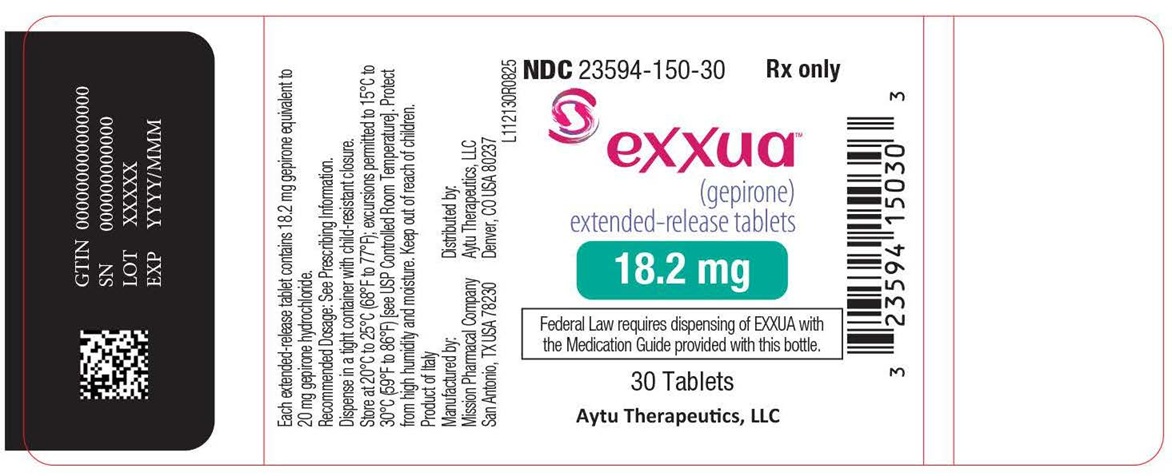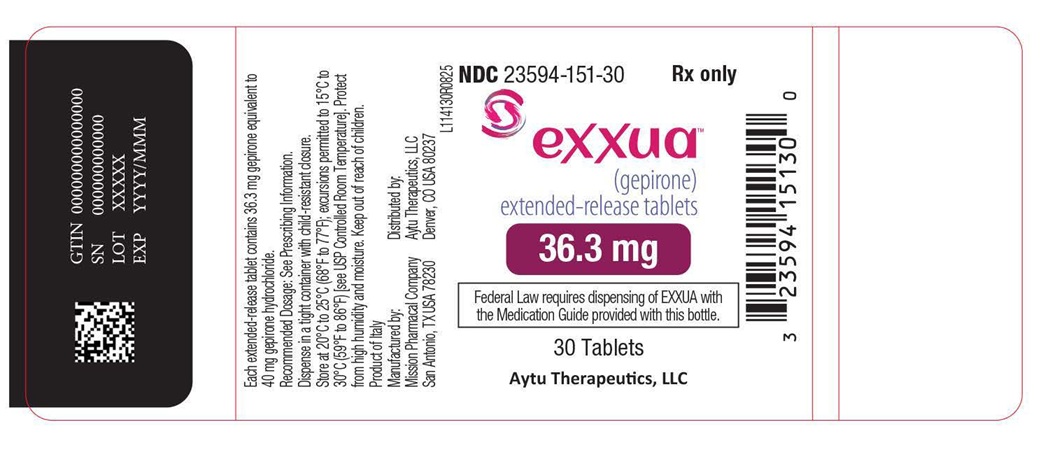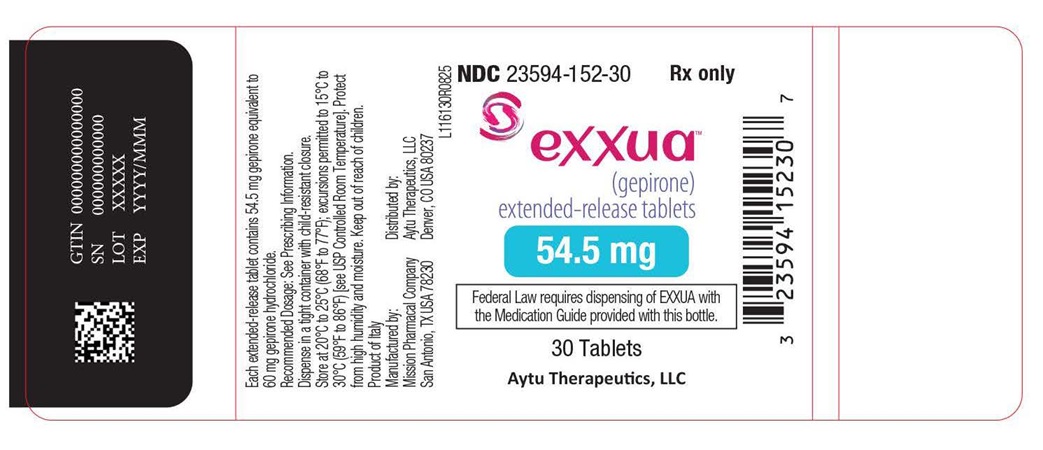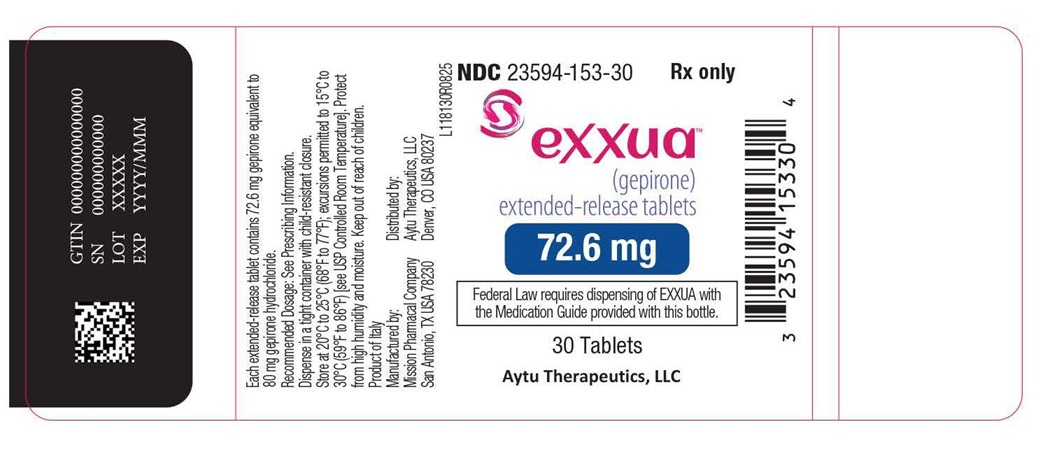 DRUG LABEL: EXXUA
NDC: 23594-150 | Form: TABLET, EXTENDED RELEASE
Manufacturer: Aytu Therapeutics, LLC
Category: prescription | Type: HUMAN PRESCRIPTION DRUG LABEL
Date: 20251016

ACTIVE INGREDIENTS: GEPIRONE HYDROCHLORIDE 18.2 mg/1 1
INACTIVE INGREDIENTS: SILICON DIOXIDE; HYPROMELLOSE, UNSPECIFIED; FERRIC OXIDE YELLOW; FERRIC OXIDE RED; MAGNESIUM STEARATE; MICROCRYSTALLINE CELLULOSE

HIGHLIGHTS OF PRESCRIBING INFORMATION

These highlights do not include all the information needed to use EXXUA™ safely and effectively. See full prescribing information for EXXUA.
EXXUA(gepirone) extended-release tablets for oral use
Initial U.S. Approval: 2023

BOXED WARNING

WARNING: SUICIDAL THOUGHTS AND BEHAVIORS

See full prescribing information for complete boxed warning.

Increased risk of suicidal thinking and behavior in pediatric and young adult patients taking antidepressants. Closely monitor for worsening and emergence of suicidal thoughts and behaviors (5.1). EXXUA is not approved for use in pediatric patients (8.4).

1 INDICATIONS AND USAGE

EXXUA is indicated for the treatment of major depressive disorder (MDD) in adults (1).

2 DOSAGE AND ADMINISTRATION

- Correct electrolyte abnormalities and perform electrocardiogram (ECG) prior to initiating treatment with EXXUA. Do not initiate EXXUA if QTc is > 450 msec (2.1).
- Perform ECGs during dosage titration and periodically during treatment (2.1).
- The recommended starting dose is 18.2 mg administered orally once daily with food at approximately the same time each day (2.2, 2.3).
- Depending on clinical response and tolerability, the dosage may be increased to 36.3 mg once daily on Day 4. Dosage may be further titrated to 54.5 mg once daily after Day 7 and to 72.6 mg once daily after an additional week (2.3).
- Geriatric patients: Recommended starting dosage is 18.2 mg once daily. Dosage may be increased to 36.3 mg after 7 days (2.4).
- Renal Impairment (creatinine clearance < 50 mL/min): Recommended starting dosage is 18.2 mg once daily. Dosage may be increased to 36.3 mg once daily after 7 days (2.5, 8.6).
- Moderate Hepatic Impairment (Child-Pugh B): Dosage may be increased to 36.3 mg once daily after 7 days (2.6, 8.7).
- Adjust EXXUA dose by 50% when a moderate CYP3A4 inhibitor is administered (2.7).

3 DOSAGE FORMS AND STRENGTHS

Extended-release tablets: 18.2 mg, 36.3 mg, 54.5 mg, and 72.6 mg (3).

4 CONTRAINDICATIONS

- Known hypersensitivity to gepirone or components of EXXUA (4).
- Prolonged QTc interval > 450 msec at baseline (4).
- Congenital long QT syndrome (4).
- Concomitant use of strong CYP3A4 inhibitors (4).
- Severe hepatic impairment (4).
- Use with an MAOI or within 14 days of stopping treatment with EXXUA. Do not use EXXUA within 14 days of discontinuing an MAOI (4).

5 WARNINGS AND PRECAUTIONS

- QT Interval Prolongation: EXXUA prolongs the QTc. Correct electrolyte abnormalities. Perform ECGs prior to initiation, during dose titration, and periodically during treatment with EXXUA. Monitor ECGs more frequently when EXXUA is used concomitantly with drugs known to prolong the QT interval, in patients who develop QTc ≥ 450 msec during treatment or are at significant risk of developing torsade de pointes. Do not escalate dosage if QTc > 450 msec (2.1, 5.2, 7).
- Serotonin Syndrome: Increased risk when co-administered with other serotonergic agents. If serotonin syndrome occurs, discontinue EXXUA and initiate supportive measures (5.3).
- Activation of Mania/Hypomania: Screen patients for bipolar disorder (5.4).

6 ADVERSE REACTIONS

Most common adverse reactions (incidence of ≥ 5% and at least twice incidence of placebo) were dizziness, nausea, insomnia, abdominal pain, and dyspepsia (6.1).

To report SUSPECTED ADVERSE REACTIONS, contact Aytu Therapeutics at 1-855-298-8246 or FDA at 1-800-FDA-1088 orwww.fda.gov/medwatch.

7 DRUG INTERACTIONS

Strong CYP3A4 inducers: Reduces EXXUA exposure. Avoid concomitant use (7).

8 USE IN SPECIFIC POPULATIONS

Pregnancy: Third trimester use may increase the risk for persistent pulmonary hypertension and symptoms of poor adaptation (respiratory distress, temperature instability, feeding difficulty, hypotonia, irritability) in the neonate (8.1).

FULL PRESCRIBING INFORMATION

BOXED WARNING

WARNING: SUICIDAL THOUGHTS AND BEHAVIORS

Antidepressants increased the risk of suicidal thoughts and behaviors in pediatric and young adult patients in short-term studies. Closely monitor all antidepressant-treated patients for clinical worsening and emergence of suicidal thoughts and behaviors [see Warnings and Precautions (5.1)] . EXXUA is not approved for use in pediatric patients [see Use in Specific Populations (8.4)]

1 INDICATIONS AND USAGE

EXXUA is indicated for the treatment of major depressive disorder (MDD) in adults.

2 DOSAGE AND ADMINISTRATION

2.1 Important Recommendations Prior to Initiating and During Treatment with EXXUA

Electrocardiogram and Electrolyte Monitoring

- Correct electrolyte abnormalities prior to initiating EXXUA. In patients with electrolyte abnormalities, or who are receiving diuretics or glucocorticoids, or who have a history of hypokalemia or hypomagnesemia, also monitor electrolytes during dose titration and periodically during treatment with EXXUA [see Warnings and Precautions (5.2)].
- Perform an electrocardiogram (ECG) prior to initiating EXXUA, during dosage titration, and periodically during treatment.
- Do not initiate EXXUA if QTc is > 450 msec at baseline.
- Monitor ECGs more frequently if EXXUA is used:
  - concomitantly with drugs known to prolong the QT interval
  - in patients who develop QTc ≥ 450 msec during treatment
  - in patients with a significant risk of developing torsade de pointes [see Warnings and Precautions (5.2) and Drug Interactions (7)].
- Do not escalate the EXXUA dosage if the QTcF is > 450 msec [see Warnings and Precautions (5.2)].

Bipolar Disorder, Mania, and Hypomania Screening

Screen patients for a personal or family history of bipolar disorder, mania, or hypomania prior to initiating treatment with EXXUA [see Warnings and Precautions (5.3)] .

2.2 Important Administration Instructions

Take EXXUA orally with food at approximately the same time each day [see Clinical Pharmacology (12.3)] . Swallow tablets whole. Do not split, crush, or chew EXXUA.

2.3 Recommended Dosage

The recommended starting dosage of EXXUA is 18.2 mg once daily. Based on clinical response and tolerability, the dosage may be increased to 36.3 mg orally once daily on Day 4 and further titrated to 54.5 mg orally once daily after Day 7 and to 72.6 mg orally once daily after an additional week. The maximum recommended daily dosage of EXXUA is 72.6 mg once daily.

2.4 Dosage Recommendations in Geriatric Patients

The recommended starting dosage of EXXUA in geriatric patients is 18.2 mg orally once daily. Based on clinical response and tolerability, the dosage may be increased to maximum recommended dosage of 36.3 mg orally once daily after Day 7 [see Use in Specific Populations (8.5) and Clinical Pharmacology (12.3)].

2.5 Recommended Dosage in Patients with Renal Impairment

The recommended starting dosage of EXXUA in patients with creatinine clearance < 50 mL/min is 18.2 mg orally once daily. Based on clinical response and tolerability, the dosage may be increased to the maximum recommended dosage of 36.3 mg orally once daily after Day 7 [see Use in Specific Populations (8.6) and Clinical Pharmacology (12.3)].

The recommended dosage in patients with creatinine clearance ≥ 50 mL/min is the same as in patients with normal renal function [see Use in Specific Populations (8.6) and Clinical Pharmacology (12.3)] .

2.6 Recommended Dosage in Patients with Hepatic Impairment

The recommended starting dose of EXXUA in patients with moderate (Child-Pugh B) hepatic impairment is 18.2 mg once daily. Based on clinical response and tolerability, the dosage may be increased to the maximum recommended dosage of 36.3 mg orally once daily after Day 7 [see Use in Specific Populations (8.7)and Clinical Pharmacology (12.3)] .

EXXUA is contraindicated in patients with severe (Child-Pugh C) hepatic impairment [see Use in Specific Populations (8.7) and Clinical Pharmacology (12.3)] .

The recommended dosage in patients with mild (Child-Pugh A) hepatic impairment is the same as patients with normal hepatic function.

2.7 Dosage Modifications for Concomitant Use with CYP3A4 Inhibitors

Reduce the EXXUA dose by 50% when used concomitantly with a moderate CYP3A4 inhibitor [see Drug Interactions (7)] .

EXXUA is contraindicated in patients receiving strong CYP3A4 inhibitors [see Contraindications (4) and Drug Interactions (7)] .

2.8 Switching a Patient to or from a Monoamine Oxidase Inhibitor (MAOI) Antidepressant

At least 14 days must elapse between discontinuation of an MAOI intended to treat depression and initiation of therapy with EXXUA. Conversely, at least 14 days must be allowed after stopping EXXUA before starting an MAOI antidepressant [see Contraindications (4) and Drug Interactions (7)] .

3 DOSAGE FORMS AND STRENGTHS

EXXUA is available as extended-release tablets in the following strengths, as gepirone base:

- 18.2 mg: pink, modified rectangular, with “FK” debossed on one side and “1” on the other side.
- 36.3 mg: off-white, modified rectangular, with “FK” debossed on one side and “7” on the other side.
- 54.5 mg: yellow, modified rectangular, with “FK” debossed on one side and “11” on the other side.
- 72.6 mg: red-brown, modified rectangular, with “FK” debossed on one side and “17” on the other side.

4 CONTRAINDICATIONS

EXXUA is contraindicated in patients:

- with known hypersensitivity to gepirone or components of EXXUA [see Adverse Reactions (6.1)] .
- with prolonged QTc interval > 450 msec at baseline [see Warnings and Precautions (5.2)].
- with congenital long QT syndrome [see Warnings and Precautions (5.2)].
- receiving concomitant strong CYP3A4 inhibitors [see Warnings and Precautions (5.2) and Drug Interactions (7)].
- with severe hepatic impairment [see Warnings and Precautions (5.2) and Use in Specific Populations (8.7)].
- taking, or within 14 days of stopping, MAOIs due to the risk of serious and possibly fatal drug interactions, including hypertensive crisis and serotonin syndrome [see Warnings and Precautions (5.3) and Drug Interactions (7)] . Starting EXXUA in a patient treated with reversible MAOIs such as linezolid or intravenous methylene blue is also contraindicated.

5 WARNINGS AND PRECAUTIONS

5.1 Suicidal Thoughts and Behaviors in Adolescents and Young Adults

In pooled analyses of placebo-controlled trials of antidepressant drugs (SSRIs and other antidepressant classes) that included approximately 77,000 adult patients, and 4,500 pediatric patients, the incidence of suicidal thoughts and behaviors in antidepressant-treated patients aged 24 years and younger was greater than in placebo-treated patients.

There was considerable variation in risk of suicidal thoughts and behaviors among drugs, but there was an increased risk identified in young patients for most drugs studied. There were differences in absolute risk of suicidal thoughts and behaviors across the different indications, with the highest incidence in patients with MDD. The drug-placebo differences in the number of cases of suicidal thoughts and behaviors per 1000 patients treated are provided in Table 1.

Table 1 Risk Differences of the Number of Patients with Suicidal Thoughts and Behaviors in the Pooled Placebo-Controlled Trials of Antidepressants in Pediatric [EXXUA is not approved for use in pediatric patients.] and Adult Patients
Age Range | Drug-Placebo Difference in Number of Patients with Suicidal Thoughts or Behaviors per 1000 Patients Treated
 | Increases Compared to Placebo
< 18 years old | 14 additional patients
18-24 years old | 5 additional patients
 | Decreases Compared to Placebo
25-64 years old | 1 fewer patient
≥ 65 years old | 6 fewer patients

It is unknown whether the risk of suicidal thoughts and behaviors in children, adolescents, and young adults extends to longer-term use, i.e., beyond four months. However, there is substantial evidence from placebo-controlled maintenance trials in adults with MDD that the use of antidepressants can delay the recurrence of depression and that depression itself is a risk factor for suicidal thoughts and behaviors.

Monitor all antidepressant-treated patients for clinical worsening and emergence of suicidal thoughts and behaviors, especially during the initial few months of drug therapy, and at times of dosage changes. Counsel family members or caregivers of patients to monitor for changes in behavior and to alert the healthcare provider. Consider changing the therapeutic regimen, including possibly discontinuing EXXUA, in patients whose depression is persistently worse, or who are experiencing emergent suicidal thoughts or behaviors.

5.2 QT Prolongation

EXXUA prolongs the QTc interval [see Clinical Pharmacology (12.2)] .

EXXUA is contraindicated in patients with congenital long QT syndrome and in patients with severe hepatic impairment or in patients receiving concomitant strong CYP3A4 inhibitors as they increase EXXUA plasma concentrations [see Contraindications (4), Drug Interactions (7), and Use in Specific Populations (8.7)] .

Do not initiate EXXUA if QTc is > 450 msec at baseline [see Dosage and Administration (2.1) and Contraindications (4)] .

Correct electrolyte abnormalities prior to EXXUA initiation. In patients with electrolyte abnormalities, who are receiving diuretics or glucocorticoids, or have a history of hypokalemia or hypomagnesemia, also monitor electrolytes during dose titration and periodically during treatment with EXXUA.

Perform an ECG prior to EXXUA initiation, during dosage titration, and periodically during treatment.

Monitor patients with ECGs more frequently:

- If EXXUA is used concomitantly with drugs known to prolong the QT interval [see Drug Interactions (7)].
- In patients who develop QTc ≥450 msec during treatment with EXXUA. Do not escalate the EXXUA dosage if QTcF is > 450 msec [see Dosage and Administration (2.1)] .
- In patients with a significant risk of developing torsade de pointes, including those with uncontrolled or significant cardiac disease, recent myocardial infarction, heart failure, unstable angina, bradyarrhythmias, uncontrolled hypertension, high degree atrioventricular block, severe aortic stenosis, or uncontrolled hypothyroidism.

Reduce the EXXUA dosage when used concomitantly with moderate CYP3A4 inhibitors, as they may increase EXXUA concentrations [see Dosage and Administration (2.7) and Drug Interactions (7)] .

5.3 Serotonin Syndrome

Concomitant use of EXXUA with SSRIs or tricyclic antidepressants may cause serotonin syndrome, a potentially life-threatening condition with changes including altered mental status, hypertension, restlessness, myoclonus, hyperthermia, hyperreflexia, diaphoresis, shivering, and tremor [see Drug Interactions (7)] .

The concomitant use of EXXUA with MAOIs is contraindicated. In addition, do not initiate EXXUA in a patient being treated with MAOIs such as linezolid or intravenous methylene blue. If it is necessary to initiate treatment with an MAOI such as linezolid or intravenous methylene blue in a patient taking EXXUA discontinue EXXUA before initiating treatment with the MAOI [see Contraindications (4) and Drug Interactions (7)] .

If concomitant use of EXXUA with other serotonergic drugs is clinically warranted, inform patients of the increased risk for serotonin syndrome and monitor for symptoms. Discontinue EXXUA and/or concomitant serotonergic drug immediately if the above symptoms occur and initiate supportive symptomatic treatment.

5.4 Activation of Mania or Hypomania

Antidepressant treatment can precipitate a manic, mixed, or hypomanic manic episode. The risk appears to be increased in patients with bipolar disorder or who have risk factors for bipolar disorder. Prior to initiating treatment with EXXUA, screen patients for a history of bipolar disorder and the presence of risk factors for bipolar disorder (e.g., family history of bipolar disorder, suicide, or depression) [see Dosage and Administration (2.1)]. EXXUA is not approved for use in treating bipolar depression.

6 ADVERSE REACTIONS

The following adverse reactions are discussed in greater detail in other sections of the labeling:

- Suicidal Thoughts and Behaviors in Adolescents and Young Adults [see Warnings and Precautions (5.1)]
- QT Prolongation [see Warnings and Precautions (5.2)]
- Serotonin Syndrome [see Warnings and Precautions (5.3)]
- Activation of Mania or Hypomania [see Warnings and Precautions (5.4)]

6.1 Clinical Trials Experience

Because clinical trials are conducted under widely varying conditions, adverse reaction rates observed in the clinical trials of a drug cannot be directly compared to rates in the clinical trials of another drug and may not reflect the rates observed in practice.

During premarketing assessment, multiple doses of EXXUA were administered to 1,976 adult patients with major depressive disorder (MDD) in controlled phase 2 and 3 clinical studies, including 1,639 patients in placebo-controlled phase 2 and 3 trials in MDD, with 237 patients exposed for over six months. The population treated with EXXUA in the pooled placebo-controlled studies ranged from 15 to 78 years of age, was 34% male and 66% female, and was 80% Caucasian, 11% Black, and 9% other race.

The adverse reaction data below are based on two placebo-controlled, flexible-dose, clinical studies (Study 1, Study 2) in which either EXXUA 18.2 mg to 72.6 mg (n=226) or placebo (n=230) was administered to adult patients with MDD during an 8-week double-blind treatment period [see Clinical Studies (14)] . Study 1 had a median age of 39 years and were 61% female, 73% Caucasian, 9% Black, 2% Asian, and 16% Other (Hispanic or Native American). Study 2 had a median age of 39 years and were 69% female, 65% Caucasian, 23% Black, 1% Asian, and 11% Hispanic.

In Study 1 and Study 2, 7% (15/226) of patients treated with EXXUA and 3% (6/230) of patients receiving placebo discontinued treatment due to an adverse reaction. The most common reactions leading to discontinuation for patients taking EXXUA were dizziness and nausea.

The most common adverse reactions (≥ 5% and twice the incidence of placebo) in EXXUA-treated patients were dizziness, nausea, insomnia, abdominal pain, and dyspepsia.

Table 2 presents the adverse reactions that occurred at an incidence of ≥ 2% of patients treated with EXXUA and at a higher incidence than in the placebo-treated patients.

Table 2 Adverse Reactions that Occurred in ≥ 2% of Patients Treated with EXXUA and Greater than the Incidence in Placebo-Treated Patients in Pooled MDD Studies (Study 1 and Study 2)
Adverse Reaction | Placebo (N=230) (%) | EXXUA (18.2 mg to 76.2 mg) (N=226) (%)
Dizziness [The following terms were combined:Dizziness=Lightheadedness, Dizziness, Dizziness Postural.Headache=Headache, Sinus Headache, Tension Headache.Feeling Sleepy or Tired=Fatigue, Sedation, Somnolence.Insomnia=Initial Insomnia, Insomnia, Middle Insomnia, Terminal Insomnia.Abdominal Pain=Abdominal Discomfort, Abdominal Pain, Abdominal Pain Upper.] | 10 | 49
Nausea | 13 | 35
Headache | 20 | 31
Feeling Sleepy or Tired | 14 | 15
Insomnia | 5 | 14
Diarrhea | 9 | 10
Upper Respiratory Tract Infection | 7 | 8
Dry Mouth | 5 | 8
Vomiting | 4 | 7
Abdominal Pain | 3 | 7
Dyspepsia | 2 | 6
Increased Appetite | 3 | 5
Constipation | 3 | 4
Nasopharyngitis | 3 | 4
Nasal Congestion | 2 | 4
Paresthesia | 1 | 4
Hyperhidrosis | 0 | 4
Palpitations | 0 | 4
Weight Increased | 1 | 3
Agitation | 0 | 3
Feeling Jittery | 0 | 3
Heart Rate Increased | 0 | 2
Lethargy | 0 | 2

Other Adverse Reactions Observed in Clinical Studies

The following is a list of adverse reactions that occurred at an incidence of < 2% in MDD patients treated with EXXUA andat least greater than placebo in Study 1 and Study 2: breast tenderness, confusional state, dyspnea, edema peripheral energy increased, feeling abnormal, hypoesthesia, poor quality sleep, and thinking abnormal.

Additional Adverse Reactions Observed in Clinical Studies

Hypersensitivity reactions including rash, pruritus, and urticaria were reported in clinical studies with EXXUA.

7 DRUG INTERACTIONS

Table 3displays clinically important drug interactions with EXXUA.

Table 3 Clinically Important Drug Interactions with EXXUA
CYP3A4 Inhibitors
Clinical Impact | Strong CYP3A4 Inhibitors Concomitant use of EXXUA with a strong CYP3A4 inhibitor increases EXXUA exposure by ~ 5-fold [see Clinical Pharmacology (12.3)] .; Moderate CYP3A4 Inhibitors; Concomitant use with a moderate CYP3A4 inhibitor increases EXXUA exposure by ~ 2.6-fold [see Clinical Pharmacology (12.3)] .
Intervention | Strong CYP3A4 Inhibitors; EXXUA is contraindicated in patients taking strong CYP3A4 inhibitors [see Dosage and Administration (2.7), Contraindications (4), and Warnings and Precautions (5.2)] .; Moderate CYP3A4 Inhibitors; If EXXUA is used with a moderate CYP3A4 inhibitor, reduce the dosage of EXXUA [see Dosage and Administration (2.7) and Warnings and Precautions (5.2)].
Monoamine Oxidase Inhibitors (MAOIs)
Clinical Impact | Concomitant use of EXXUA with MAOIs increases the risk of serotonin syndrome.
Intervention | EXXUA is contraindicated in patients taking MAOIs, including MAOIs such as linezolid or intravenous methylene blue or in patients who have taken MAOIs within the preceding 14 days.; Allow at least 14 days after stopping EXXUA before starting an MAOI [see Dosage and Administration (2.8), Contraindications (4), and Warnings and Precautions (5.3)].
Drugs that Prolong the QTc Interval
Clinical Impact | Concomitant use of drugs that prolong the QTc interval may add to the QTc prolonging effects of EXXUA and increase the risk of cardiac arrhythmias.
Intervention | Monitor patients with ECGs more frequently if EXXUA is administered with other drugs known to prolong QT interval [see Warnings and Precautions (5.2)] .
CYP3A4 Inducers
Clinical Impact | Concomitant use of EXXUA with a strong CYP3A4 inducer reduces EXXUA exposure by 20- to 29-fold [see Clinical Pharmacology (12.3)] .
Intervention | Avoid concomitant use of EXXUA in patients taking strong CYP3A4 inducers.
Other Serotonergic Drugs
Clinical Impact | Concomitant use of EXXUA and serotonergic drugs increases the risk of serotonin syndrome.
Intervention | Monitor for symptoms of serotonin syndrome when EXXUA is used concomitantly with other drugs that may affect the serotonergic neurotransmitter systems. If serotonin syndrome occurs, consider discontinuation of EXXUA and/or concomitant serotonergic drug [see Warnings and Precautions (5.3)] .

8 USE IN SPECIFIC POPULATIONS

8.1 Pregnancy

Pregnancy Exposure Registry

There is a pregnancy exposure registry that monitors pregnancy outcomes in women exposed to antidepressants, including EXXUA, during pregnancy. Healthcare providers are encouraged to register patients by calling the National Pregnancy Registry for Antidepressants at 1-866-961-2388 or visiting online at https://womensmentalhealth.org/research/pregnancyregistry/antidepressants/.

Risk Summary

Based on animal reproduction studies, gepirone has been shown to have adverse effects on embryo/fetal and postnatal development. In rats, increased mortality during the first 4 days after birth and persistent reduction in body weight through lactation and weaning were observed at all doses and increased still births were seen with a no observed adverse effect level (NOAEL) at 3 times the maximum recommended human dose (MRHD) on a mg/m^2basis. In embryofetal development studies in rats and rabbits, decreased embryofetal growth, body weights and lengths, with accompanying skeletal variations were seen with a NOAEL at 9 and 12 times the MRHD on a mg/m^2basis, respectively (see Data).There are insufficient clinical data on gepirone use during pregnancy to evaluate for a drug-associated risk of major birth defects, miscarriage, or other adverse maternal or fetal outcomes. There are clinical considerations regarding neonates exposed to serotonergic antidepressants during the third trimester of pregnancy (see Clinical Considerations and Data).There are risks associated with untreated depression during pregnancy (see Clinical Considerations).Consider if the risks outweigh the benefits of treatment with gepirone during pregnancy.

The background risk of major birth defects and miscarriage for the indicated population is unknown. In the U.S. general population, the estimated background risk of major birth defects and miscarriage in clinically recognized pregnancies is 2 to 4% and 15 to 20%, respectively.

Clinical Considerations

Disease-associated Maternal and/or Embryofetal Risk

Women who discontinue antidepressants during pregnancy are more likely to experience a relapse of major depression than women who continue antidepressants. This finding is from a prospective, longitudinal study of 201 pregnant women with a history of major depressive disorder who were euthymic and taking antidepressants at the beginning of pregnancy. Consider the risk of untreated depression when discontinuing or changing treatment with antidepressant medication during pregnancy and postpartum.

Fetal/Neonatal Adverse Reactions

Neonates exposed to other serotonergic antidepressants in the third trimester have developed complications requiring prolonged hospitalization, respiratory support, and tube feeding. Complications can arise immediately upon delivery. Reported clinical findings have included respiratory distress, cyanosis, apnea, seizures, temperature instability, feeding difficulty, vomiting, hypoglycemia, hypotonia, hypertonia, hyperreflexia, tremors, jitteriness, irritability, and constant crying. These findings are consistent with either a direct toxic effect of SSRIs or possibly a drug discontinuation syndrome. It should be noted that, in some cases, the clinical picture is consistent with serotonin syndrome [See Warnings and Precautions (5.3)].

Data

Human Data

Exposure during late pregnancy to serotonergic antidepressants may have an increased risk for persistent pulmonary hypertension of the newborn (PPHN). PPHN occurs in 1- 2 per 1,000 live births in the general population and is associated with substantial neonatal morbidity and mortality.

Animal Data

In embryofetal development studies, oral administration of gepirone to pregnant rats (75, 150, and 300 mg/kg) or pregnant rabbits (50, 100, and 200 mg/kg) during the period of organogenesis resulted in decreased embryofetal growth, body weights and lengths, with accompanying skeletal variations at mid and high doses; the mid doses are 18 and 24 times the MRHD on a mg/m^2basis in rats and rabbits, respectively. No malformations were seen in these studies. The developmental NOAEL was 9 and 12 times the MRHD on a mg/m^2basis in rats and rabbits, respectively.

When pregnant rats were treated with gepirone (10, 20, and 40 mg/kg) from late gestation through weaning, decreased birth weights were seen at mid and high doses; the mid dose is twice the MRHD. Increased offspring mortality during the first 4 days after birth and persistent reduction in body weight were observed at all doses; the lowest dose is approximately equal to the MRHD on a mg/m^2basis. The no-effect dose for fetal effects was not determined in this study.

When gepirone was administered orally to male and female rats prior to and throughout mating, gestation, and lactation at doses of 5, 27, 64, and 150 mg/kg/day, increased still births were seen at ≥ 64 mg/kg. Early postnatal mortality was increased at 150 mg/kg (18 times the MRHD on a mg/m^2basis). The NOAEL (27 mg/kg) for still births was associated with a maternal dose 3 times the MRHD on a mg/m^2basis. Fetal weights were decreased at 27 mg/kg (3 times the MRHD on a mg/m^2basis) and fetal lengths were decreased at 64 mg/kg (8 times the MRHD on a mg/m^2basis) and above. Pup weights were decreased at birth, throughout lactation and weaning, and until at least 14 weeks of age, with delays of some developmental landmarks, at 64 mg/kg and above. The NOAEL for growth and development (5 mg/kg) was associated with a maternal dose below the MRHD on a mg/m^2basis.

8.2 Lactation

Risk Summary

There are no data on the presence of gepirone in human milk, the effects on the breastfed infant, or the effects on milk production. Gepirone is present in rat milk .When a drug is present in animal milk, it is likely that the drug will be present in human milk. There are reports of breastfed infants exposed to other serotonergic antidepressants experiencing irritability, restlessness, excessive somnolence, decreased feeding, and weight loss (see Clinical Considerations).The developmental and health benefits of breastfeeding should be considered along with the mother’s clinical need for EXXUA and any adverse effects on the breastfed infant from EXXUA or from the underlying maternal condition.

Clinical Considerations

Monitor breastfeeding infants for adverse reactions, such as irritability, restlessness, excessive somnolence, decreased feeding, and weight loss.

8.4 Pediatric Use

The safety and effectiveness of EXXUA in pediatric patients have not been established for the treatment of MDD.

Efficacy was not demonstrated in two 8-week, randomized, placebo-controlled trials in 426 pediatric patients 7 to 17 years of age with MDD. The primary efficacy endpoint was change from double-blind baseline to Week 8 on the Children’s Depression Rating Scale-Revised (CDRS-R) measure. The effect of treatment with EXXUA was not significantly different from placebo. In the pediatric trial patients, there was a higher occurrence of vomiting in pediatric patients (13%) compared to adults (6.6%).

Antidepressants, such as EXXUA, increase the risk of suicidal thoughts and behaviors in pediatric patients [see Warnings and Precautions (5.1)].

Juvenile Animal Toxicity Data

In a juvenile animal study, male and female rats were treated with gepirone once daily with oral doses of 0, 10, 40, and 70 mg/kg, from postnatal day 14 to 42. Increased motor activity and impaired performance in the Morris water maze were observed at 40 and 70 mg/kg after a two-week recovery period. The no observed adverse effect level (NOAEL) for the neurobehavioral development effect was 10 mg/kg. When the animals were mated after a 3-week recovery period, increased pre-implantation loss was observed for mated pairs treated with 70 mg/kg. The NOAEL for this finding was 40 mg/kg/day.

8.5 Geriatric Use

Of the 1,639 patients exposed to EXXUA in placebo-controlled clinical studies of MDD, 0.7% (12 patients) were 65 years of age or older and 0.2% (3 patients) were 75 years or older.

Geriatric patients (65 to 81 years of age) had higher EXXUA AUC and Cmaxvalues than younger adult (18 to 40 years of age) patients [see Clinical Pharmacology (12.3)] . The maximum recommended daily dosage of EXXUA in geriatric patients is lower than in younger adult patients [see Dosage and Administration (2.4)] .

8.6 Renal Impairment

In patients with creatinine clearance < 50 mL/min, the metabolism and excretion of EXXUA and some of its major metabolites were decreased [see Clinical Pharmacology (12.3)] . The maximum recommended daily dosage of EXXUA in patients with a creatinine clearance < 50 mL/min is lower than in patients with normal renal function [see Dosage and Administration (2.5)] . The recommended dosage in patients with a creatinine clearance ≥ 50 mL/min is the same as in patients with normal renal function [see Dosage and Administration (2.5)] .

8.7 Hepatic Impairment

In patients with mild (Child-Pugh A) hepatic impairment to moderate (Child-Pugh B) hepatic impairment, the metabolism of EXXUA and its major metabolites was decreased [see Clinical Pharmacology (12.3)] . The maximum recommended dosage of EXXUA in patients with moderate hepatic impairment is lower than in patients with normal hepatic function [see Dosage and Administration (2.6)] . The recommended dosage in patients with mild hepatic impairment is the same as in patients with normal hepatic function.

EXXUA is contraindicated in patients with severe (Child-Pugh C) hepatic impairment [see Warnings and Precautions (5.2)and Clinical Pharmacology (12.3)] .

10 OVERDOSAGE

In clinical studies, cases of acute ingestions up to 454 mg (6.25 times the maximum recommended dose) of EXXUA alone or in combination with other drugs, were reported. Signs and symptoms reported with overdose of EXXUA at doses up to 454 mg included vomiting and transient incomplete bundle branch block; an unknown dose of EXXUA produced altered level of consciousness and a 60-second convulsion.

No specific antidotes for EXXUA are known.

Consider contacting the Poison Help line (1-800-222-1222) or a medical toxicologist for additional overdose management recommendations.

11 DESCRIPTION

EXXUA contains gepirone, in the salt form as gepirone hydrochloride (HCl). The chemical name is 2,6- piperidinedione,4,4-dimethyl-1-[4-[4-(2-pyrimidinyl)-1-piperazinyl]butyl]-, monohydrochloride. The molecular weight of gepirone HCl is 395.93 and the structural formula is as follows:

Gepirone HCl is a white to off-white crystalline powder, which is readily soluble in water.

EXXUA is supplied as extended-release tablets for oral administration. Each extended-release tablet contains 18.2 mg, 36.3 mg, 54.5 mg, or 72.6 mg, gepirone equivalent to 20 mg, 40 mg, 60 mg, or 80 mg of gepirone HCl respectively. The extended-release tablets also contain the following inactive ingredients: colloidal silicon dioxide, Hypromellose, iron oxide (red and/or yellow colorants), magnesium stearate, and microcrystalline cellulose.

12 CLINICAL PHARMACOLOGY

12.1 Mechanism of Action

The mechanism of the antidepressant effect of EXXUA is not fully understood but is thought to be related to its modulation of serotonergic activity in the CNS through selective agonist activity at 5HT1A receptors.

12.2 Pharmacodynamics

The pharmacological activity of gepirone is attributed to the parent drug and its major metabolites 3’-OH-gepirone and 1-PP. Gepirone and its 3’-OH metabolite bind to 5HT1A receptors (Ki = 38 nM and 58 nM, respectively), where they act as agonists, while the 1-PP metabolite binds to alpha2 receptors (Ki = 42 nM).

Cardiac Electrophysiology

In a thorough QT study, the largest mean increase in baseline- and placebo-corrected QTc interval with administration of 100 mg per day immediate-release formulation of gepirone was 18.4 msec (upper 90% confidence interval [CI] = 22.7 ms) on Day 1 and 16.1 msec (upper 90% CI = 20.7 ms) on Day 7. The exposure in this study was 2-fold the exposure of the maximum recommended dose [see Dosage and Administration (2.1) and Warnings and Precautions (5.2)] .

12.3 Pharmacokinetics

The pharmacokinetics of EXXUA are linear and dose proportional from 18.2 mg to 72.6 mg. Steady-state plasma concentration are typically achieved within two to four days of daily dosing.

Absorption

The absolute bioavailability is 14% to 17%. The maximal plasma EXXUA concentration (Cmax) after dosing is reached within 6 hours post dose (Tmax).

Effect of Food

After a high fat meal, Tmaxis reached at 3 hours. A significant effect of food has been observed on the peak plasma concentration (Cmax) of EXXUA and, to a lesser extent, on the total exposure (AUC0-tlast, AUC0-∞) to EXXUA. The magnitude of the food-effect was dependent of the fat content of the meal. The systemic exposure of EXXUA and major metabolites was consistently higher under fed conditions as compared to the fasted state. Gepirone Cmaxafter intake of low-fat (~ 200 calories) breakfast was 27% higher, after medium-fat (~500 calories) breakfast 55% higher and after a high-fat (~ 850 calories) breakfast 62% higher as compared to the fasted state. The AUC after intake of low-fat breakfast was about 14% higher, after a medium-fat breakfast 22% higher and after a high-fat breakfast 32 to 37% higher as compared to the fasted state. The effect of varying amounts of fat on Cmaxand AUC of the major metabolites 3’-OH-gepirone and 1-PP were similar to that found for gepirone [see Dosage and Administration (2.2)].

Distribution

The apparent volume of distribution of EXXUA is approximately 94.5L. The in vitroplasma protein binding in human is 72% and is not concentration dependent. The in vitroplasma proteinbinding for metabolite 3’-OH-gepirone is 59%and 42% for 1-PP.

Elimination

The mean terminal half-life is approximately 5 hours.

Metabolism

EXXUA is extensively metabolized and both major metabolites 1-PP and 3’-OH-gepirone are present in plasma in higher concentrations than the parent compound. CYP3A4 is the primary enzyme catalyzing the metabolism of EXXUA to its major pharmacologically active metabolites.

Excretion

Following a single oral dose of [^14C]-labeled gepirone, approximately 81% and 13% of the administered radioactivity was recovered in the urine and feces, respectively as metabolites. 60% of the gepirone was eliminated in the urine within the first 24 hours. The presence of hepatic or renal impairment did affect the apparent clearance of EXXUA.

Specific Populations

Exposures of gepirone in specific populations are summarized in Figure 1 [see Dosage and Administration (2.3,2.4, 2.5), Contraindications (4), and Use in Specific Populations (8.5,8.6,8.7)] .

Figure 1 Effects of Specific Populations on the Pharmacokinetics of Gepirone

Gepirone dose: 36.3 mg in renal, 18.2 mg in hepatic; steady-state at 18.2 mg for race and 18.2-72.6 mg for age.

Data are GMRs and 90% CIs, except for Age groups (arithmetic mean ratios). AUC = area under the plasma concentration-time curve; CI = confidence interval; Cmax= maximum plasma concentration; GMR = geometric mean ratio.

Drug Interactions Studies

In Vivo Studies

The effect of co-administered drugs on the pharmacokinetics of gepirone is summarized in Figure 2 [see Dosage and Administration (2.6) and Drug Interactions (7)] .

Figure 2 Effect of Co-Administered Drugs on the Pharmacokinetics of Gepirone

Rifampin

The effect of multiple oral dosing of potent cytochrome P450 3A4 inducer rifampin on the steady-state pharmacokinetics of EXXUA and its major metabolites 1-PP and 3’-OH-gepirone was investigated in 24 subjects. Combined therapy with rifampin (600 mg daily) and EXXUA (20 mg for two days, then 40 mg daily) decreased Cmaxand AUC0-24 of EXXUA 20 times (EXXUA Cmaxalone 9.63 ng/mL, with rifampin 0.491 ng/mL) and 29 times (EXXUA AUC0-24 alone 123 ng·hr/mL, with rifampin 4.19 ng·hr/mL), respectively. The Cmaxand AUC0-24 of 3’-OH gepirone were decreased 2.5 times (3’-OH gepirone Cmaxalone 23.0 ng/mL, with rifampin 9.30 ng/mL) and three times (3’-OH gepirone AUC0-24 alone 371 ng·hr/mL, with rifampin 126 ng·hr/mL), respectively. There was no effect on the pharmacokinetics of 1-PP (1-PP Cmaxalone 6.37 ng/mL, with rifampin 6.02 ng/mL; 1-PP AUC0-24 alone 92.5 ng·hr/mL, with rifampin 81.1 ng·hr/mL).

Glyburide

Under steady-state conditions for glyburide, the addition of 36.3 mg daily of EXXUA for six days in 16 patients with stable Type II diabetes resulted in statistically significantly lower AUC (glyburide AUC0-12alone 574.8 ng·h/mL, with EXXUA 483.0 ng·h/mL) and Cmax(glyburide Cmaxalone 121.0 ng/mL, with EXXUA 96.6 ng/mL) values for glyburide.

Drugs that Interfere with Hemostasis

Following coadministration of stable dose of warfarin (INR 1.4 to 2.0) with multiple daily doses of EXXUA, no significant effect was observed in INR, prothrombin values, or total warfarin (protein bound plus free drug) pharmacokinetics for warfarin.

Drugs that Interfere with Protein Binding

Gepirone is not highly bound to plasma protein and is not likely to be involved in interactions due to altered protein binding. In a clinical study with coadministration of EXXUA (18.2 mg) and warfarin, a highly protein-bound drug, no significant change in international normalized ratio (INR) was observed.

In Vitro Studies

Gepirone at concentrations of 0.5, 5, and 50 ng/mL was shown to have no significant impact on the plasma protein binding of chlorpromazine, desipramine, diazepam, phenytoin, prazosin, propranolol, verapamil, or warfarin. The binding of digoxin and haloperidol were decreased (at maximum) by 5% and 9%, respectively. The plasma protein binding of lidocaine appeared to be increased by 4.9% in the presence of gepirone.

Alcohol:An in vitrostudy showed dissolution rate for both 18.2 mg and 72.6 mg gepirone ER tablets decreased slightly as ethanol concentration increased in 0.01N HCl and 0.1N HCl at 0%, 5%, 10%, 20% and 40% alcohol. At 20 hours and 40% alcohol, approximately (mean) 76.8% and 80.7% were dissolved for the 18.2 mg and 72.6 mg gepirone ER tablets, respectively.

Transporter Systems: EXXUA and its metabolites are unlikely to cause clinically significant inhibition of the following transporters based on in vitrodata: P-gp, BCRP, BSEP, OATP1B1, OATP1B3, OAT1, OAT3, OCT2, MATE1, and MATE2-K. As such, no clinically relevant interactions with drugs metabolized/transported by these CYP enzymes or transporters would be expected.

Enzyme systems: In addition, EXXUA has not been shown to be an inhibitor or inducer of any of the cytochrome P450 enzymes [see Clinical Pharmacology (12.3)] . Chronic administration of EXXUA is unlikely to induce the metabolism of drugs metabolized by these CYP isoforms.

13 NONCLINICAL TOXICOLOGY

13.1 Carcinogenesis, Mutagenesis, Impairment of Fertility

Carcinogenesis

No evidence of carcinogenic potential was observed in lifetime carcinogenicity studies performed in rats and mice at doses up to 43.6 and 317.8 mg/kg/day, respectively. These doses are approximately 6 and 18 times the maximum recommended human dose (MRHD), respectively, on a mg/m^2basis.

Mutagenicity

Gepirone showed no mutagenicity in three different in vitrogenotoxicity assays (bacterial gene mutation, mammalian gene mutation, or DNA repair). No clastogenicity was observed in a rat micronucleus assay.

Impairment of Fertility

When gepirone was administered orally to male and female rats prior to and throughout mating at daily doses of 5, 27, 64, and 150 mg/kg, the latency to mating was increased at doses of 64 mg/kg (8 times the MRHD on a mg/m2 basis) and above.

14 CLINICAL STUDIES

The efficacy of EXXUA for the treatment for major depressive disorder (MDD) in adults was evaluated in two eight-week randomized, double-blind, placebo-controlled, flexible-dose studies in adults (age 18 to 69 years) meeting Diagnostic and Statistical Manual of Mental Disorders (DSM-IV) criteria for MDD.

In Study 1, adult patients (18 to 69 years) who met DSM-IV diagnostic criteria for MDD were included in the trial. Patients in Study 1 had a median age of 39 years and were 61% female, 73% Caucasian, 9% Black, 2% Asian, and 16% Other (Hispanic or Native American). After an initial dosage of 18.2 mg once daily, the dosage was titrated to 36.3 mg once daily on Day 4 of treatment. The dosage could then be increased to 54.5 mg once daily after Day 7, and to 72.6 mg once daily after an additional 7 days. In patients that received EXXUA, the final daily dose of EXXUA was 72.6 mg in 64% of patients, 54.5 mg in 20% of patients, and 36.3 mg in 17% of patients.

In Study 2, adult patients (18 to 64 years) who met DSM-IV diagnostic criteria for MDD were included in the trial. Patients in Study 2 had a median age of 39 years and were 69% female, 65% Caucasian, 23% Black, 1% Asian, and 11% Hispanic. After an initial dosage of 18.2 mg daily, the dosage was titrated to 36.3 mg daily on Days 4 to 7 of treatment. The dosage could then be increased to 54.5 mg daily after Day 7, and to 72.6 mg daily after an additional 7 days. In patients that received EXXUA, the final daily dose of EXXUA was 72.6 mg in 66% of patients, 54.5 mg in 22% of patients, 36.3 mg in 10% of patients, and 18.2 mg in 2% of patients.

In Study 1 and Study 2, the primary efficacy measure was the change from baseline in the Hamilton Depression Rating Scale (HAMD-17) total score at Week 8. In both studies, patients in the EXXUA groups experienced statistically significantly greater improvement on the primary endpoint compared to patients in the placebo groups (see Table 4).

Table 4 Results for the Primary Endpoint: Change from Baseline in the HAMD-17 Total Score at Week 8 in Adult Patients with MDD (Study 1 and Study 2)
Study Number | Treatment Group | N | Mean Baseline Score (SD) | LS Mean CFB (SE) | Placebo-subtracted Difference (95% CI)
1 | EXXUA (18.2 to 72.6 mg/day) | 101 | 22.7 (2.45) | -9.04 (0.78) | -2.47 (-4.41, -0.53)
1 | Placebo | 103 | 22.8 (2.51) | -6.75 (0.77)
2 | EXXUA (18.2 to 72.6 mg/day) | 116 | 23.9 (2.69) | -10.22 (0.75) | -2.45 (-4.47, -0.43)
 | Placebo | 122 | 24.2 (2.93) | -7.96 (0.73)
N= number of patients in the primary efficacy analysis set; CFB=Change from baseline; LS=Least Squares; SD=Standard Deviation; SE=Standard Error
In Study 1, the final dose of EXXUA was 72.6, 54.5, and 36.3 mg/day in 64%, 20%, and 17% of patients, respectively.
In Study 2, the final dose of EXXUA was 72.6, 54.5, 36.3, and 18.2 mg/day in 66%, 22%, 10%, and 2% of patients, respectively.

The change from baseline in HAMD-17 total score by week compared to placebo for Study 2 is shown in Figure 3.

Figure 3 Mean Change from Baseline in HAMD-17 Total Score by Treatment Week (Study 2)

16 HOW SUPPLIED

How Supplied

EXXUA (gepirone) extended-release tablets are supplied in bottles of 30 with child-resistant caps and in four dosage strengths:

- 18.2-mg Tablets –pink, modified rectangular, with “FK” debossed on one side and “1” on the other side.
  Bottles of 30 NDC 23594-150-30
- 36.3-mg Tablets –off-white, modified rectangular, with “FK” debossed on one side and “7” on the other side.
  Bottles of 30 NDC 23594-151-30
- 54.5-mg Tablets –yellow, modified rectangular, with “FK” debossed on one side and “11” on the other side.
  Bottles of 30 NDC 23594-152-30
- 72.6-mg Tablets –red-brown, modified rectangular, with “FK” debossed on one side and “17” on the other side.
  Bottles of 30 NDC 23594-153-30

EXXUA (gepirone) extended-release tablets Titration Pack is supplied with child-resistant cap in the following configuration:

- 18.2-mg Tablets –pink, modified rectangular, with “FK” debossed on one side and “1” on the other side.
  Bottles of 32 NDC 23594-150-32

Storage

Store at 20°C to 25°C (68°F to 77°F); excursions are permitted between 15°C to 30°C (59°F to 86°F) [see USP Controlled Room Temperature]. Protect from high humidity and moisture.

17 PATIENT COUNSELING INFORMATION

Advise the patient to read the FDA-approved patient labeling (Medication Guide).

Suicidal Thoughts and Behaviors

Advise patients and caregivers to look for the emergence of suicidal ideation and behavior, especially during early treatment and when the dose is adjusted up or down and instruct them to report such symptoms to their healthcare provider [see Box Warningand Warnings and Precautions (5.1)] .

QT Prolongation

Inform patients to consult their physician immediately if they feel faint, lose consciousness, or have heart palpitations [see Warnings and Precautions (5.2)] . Advise patients to inform their healthcare provider if they are taking, or plan to take, any prescription or over-the-counter medications because there is an increased risk for drug interactions with EXXUA [see Drug Interactions (7)].

Serotonin Syndrome

Caution patients about the risk of serotonin syndrome, particularly with the concomitant use of EXXUA with SSRIs or tricyclic antidepressants. Instruct patients to contact their health care provider or report to the emergency room if they experience signs or symptoms of serotonin syndrome [see Warnings and Precautions (5.3) and Drug Interactions (7)] .

Activation of Mania or Hypomania

Advise patients to observe for signs of activation of mania or hypomania and instruct them to report such symptoms to their healthcare provider [see Warnings and Precautions (5.4)] .

Administration Information

Advise patients to swallow EXXUA whole and not to split, chew, or crush the tablets. Advise patients to take EXXUA at approximately the same time every day with food [see Dosage and Administration (2.2)].

Pregnancy

Advise pregnant women to notify their healthcare provider if they become pregnant or intend to become pregnant during treatment with EXXUA.

Advise patients that there is a pregnancy registry that monitors pregnancy outcomes in women exposed to EXXUA during pregnancy .

Advise patients that EXXUA use late in pregnancy may lead to an increased risk for neonatal complications requiring prolonged hospitalization, respiratory support, tube feeding, and/or persistent pulmonary hypertension of the newborn (PPHN) [see Use in Specific Populations (8.1)].

Lactation

Advise breastfeeding individuals using EXXUA to monitor infants for excess sedation, restlessness, agitation, poor feeding and poor weight gain and to see medical care if they notice these signs [see Use in Specific Populations (8.2)].

Product of Italy

Manufactured by:

Mission Pharmacal Company

San Antonio, TX USA 78230

Distributed by:

Aytu Therapeutics, LLC

Denver, CO USA 80237

L112130R0825

MEDICATION GUIDE

MEDICATIONGUIDE
EXXUA™(EKS-shoo-uh)
(gepirone)
extended-release tablets

What is the most important information I should know about EXXUA?
EXXUA may cause serious side effects, including:

- Increased risk of suicidal thoughts and actions.EXXUA and other antidepressant medicines may increase suicidal thoughts and actions in some people 24 years of age and younger, especially within the first few months of treatment or when the dose is changed. EXXUA is not for use in children.
  - Depression or other mental illnesses are the most important causes of suicidal thoughts or actions.

How can I watch for and try to prevent suicidal thoughts and actions in myself or family member?

- Pay close attention to any changes, especially sudden changes in mood, behavior, thoughts, or feelings or if you develop suicidal thoughts or actions. This is very important when an antidepressant medicine is started or when the dose is changed.
- Call your healthcare provider right away to report new or sudden changes in mood, behavior, thoughts, or feelings or if you develop suicidal thoughts or actions.
- Keep all follow-up visits with your healthcare provider as scheduled. Call your healthcare provider between visits as needed, especially if you have concerns about symptoms.

Call a healthcare provider or get emergency medical help right away if you or your family member has any of the following symptoms, especially if they are new, worse, or worry you:

- thoughts about suicide or dying
- new or worse depression
- feeling very agitated or restless
- trouble sleeping (insomnia)
- acting aggressive, being angry, or violent
- an extreme increase in activity and talking (mania)

- attempts to commit suicide
- new or worse anxiety
- panic attacks
- new or worse irritability
- acting on dangerous impulses
- other unusual changes in behavior or mood

What is EXXUA?
EXXUA is a prescription medicine used to treat adults with a certain type of depression called major depressive disorder (MDD).

It is not known if EXXUA is safe and effective in children.

- have a prolonged QTc interval greater than 450 msec or congenital long QT syndrome.
- are taking medicines known as strong CYP34A inhibitors. Ask your healthcare provider if you are not sure if you are taking one of these medicines.
- have severe liver problems.
- are taking, or have stopped taking within the last 14 days, a medicine called a monoamine oxidase inhibitor (MAOI), including the antibiotic linezolid or intravenous methylene blue. Ask your healthcare provider or pharmacist if you are not sure if you take an MAOI, including the antibiotic linezolid or intravenous methylene blue.

Do not take EXXUA if you:

- are allergic to EXXUA or any of the ingredients in EXXUA. See the end of this Medication Guide
  for a complete list of ingredients in EXXUA.
- have a prolonged QTc interval greater than 450 msec or congenital long QT syndrome.
- are taking medicines known as strong CYP34A inhibitors. Ask your healthcare provider if you
  are not sure if you are taking one of these medicines.
- have severe liver problems.
- are taking, or have stopped taking within the last 14 days, a medicine called a monoamine
  oxidase inhibitor (MAOI), including the antibiotic linezolid or intravenous methylene blue. Ask
  your healthcare provider or pharmacist if you are not sure if you take an MAOI, including the
  antibiotic linezolid or intravenous methylene blue.

Do not start taking an MAOI for at least 14 days after you have stopped treatment with EXXUA.

Before taking EXXUA, tell your healthcare provider about all your medical conditions, including if you:

- have, or have a family history of, bipolar disorder, mania, or hypomania
- have any heart problems, including heart failure, recent heart attack, high blood pressure, a slow heart rate or heart rhythm problems
- have a history of electrolyte problems, including low potassium or low magnesium
- have liver problems
- have kidney problems
- are pregnant or plan to become pregnant. EXXUA may harm your unborn baby. Taking EXXUA during the third trimester of pregnancy may cause the baby to have withdrawal symptoms, or breathing, temperature control, feeding, or other problems after birth. Talk to your healthcare provider about the risks to the baby if you take EXXUA during pregnancy.
  - Tell your healthcare provider if you become pregnant or think you may be pregnant during treatment with EXXUA.
  - There is a pregnancy registry for females who are exposed to EXXUA during pregnancy. The purpose of the registry is to collect information about the health of females exposed to EXXUA and their baby. If you become pregnant during treatment with EXXUA, talk to your healthcare provider about registering with the National Pregnancy Registry for Antidepressants at 1-866- 961-2388 or visit online at https://womensmentalhealth.org/clinical-and-research-programs/ pregnancyregistry/antidepressants/.
- are breastfeeding or plan or breastfeed. It is not known if EXXUA passes into your breast milk. Talk to your healthcare provider about the best way to feed your baby during treatment with EXXUA.
- if you breastfeed during treatment with EXXUA, call your healthcare provider if the baby develops sleepiness or fussiness, or is not feeding or gaining weight well.

Tell your healthcare provider about all the medicines you take,including prescription and
medicines, vitamins, and herbal supplements

EXXUA and other medicines may affect each other causing possible serious side effects. EXXUA
may affect the way other medicines work and other medicines may affect the way EXXUA works.

Especially tell your healthcare provider if you takediuretics, corticosteroids, medicines used
to treat migraine headache called triptans, or medicines used to treat mood, anxiety, psychotic or
thought disorders, including selective serotonin reuptake inhibitors (SSRIs), serotonin norepinephrine
reuptake inhibitors (SNRIs), or tricyclic antidepressants.

Your healthcare provider can tell you if it is safe to take EXXUA with your other medicines. Do not
start or stop any other medicines during treatment with EXXUA without talking to your healthcare
provider first.

Know the medicines you take. Keep a list of them to show to your healthcare provider and pharmacist
when you get a new medicine.

How should I take EXXUA?

- Take EXXUA exactly as your healthcare provider tells you to take it. Do not change the dose or
  stop taking EXXUA without first talking to your healthcare provider.
- Take EXXUA 1 time each day with food at about the same time each day.
- Swallow EXXUA tablets whole. Do not break, chew, crush, or dissolve tablets.
- If you miss a dose, take it as soon as you remember. If it is time for your next dose, skip the
  missed dose and take only your regularly scheduled dose. Do not take 2 doses at the same time
  to make up for a missed dose.
- If you take too much EXXUA, call your healthcare provider or Poison Help Line at 1-800-222-1222 or go to the nearest hospital emergency room right away.

What are the possible side effects of EXXUA?

EXXUA may cause serious side effects, including:

- See “What is the most important information I should know about EXXUA”?
- Changes in the electrical activity of your heart called QT prolongation.QT prolongation
  can cause irregular heartbeats that can be life-threatening or lead to death. Your healthcare
  provider will check the electrical activity of your heart with a test called an electrocardiogram
  (ECG) and will also do blood tests to check your levels of body salts (electrolytes) before and
  during treatment with EXXUA. Your healthcare provider may check your electrolytes more often
  during treatment if you have heart failure, a slow heart rate, abnormal levels of electrolytes in
  your blood, or if you take a medicine that can prolong the QT interval of your heartbeat. Tell your
  healthcare provider right away if you have an irregular heartbeat or feel dizzy, lightheaded, or
  faint during treatment with EXXUA.
- Serotonin syndrome.A potentially life-threatening problem called serotonin syndrome can
  happen when EXXUA is taken with certain other medicines. See “Do not take EXXUA if you:”.
  Call your healthcare provider or go to the nearest hospital emergency room right away if
  you have any of the following signs and symptoms of serotonin syndrome:

- agitation
- confusion
- fast heartbeat
- sweating
- flushing
- seizures
- nausea, vomiting, and diarrhea

- seeing or hearing things that are not real
  (hallucinations)
- coma
- blood pressure changes
- shaking (tremors), stiff muscles, or muscle
  twitching
- dizziness
- high body temperature (hyperthermia)
- loss of coordination

- Manic episodes.Manic episodes may happen in people with bipolar disorder who take EXXUA.
  Symptoms may include:

- greatly increased energy
- racing thoughts
- unusually grand ideas
- talking more or faster than usual

- severe problems sleeping
- reckless behavior
- excessive happiness or irritability

The most common side effects of EXXUA include:dizziness, nausea, headache, trouble sleeping,
stomach (abdominal) pain, and upset stomach.

These are not all the possible side effects of EXXUA.

Call your doctor for medical advice about side effects. You may report side effects to FDA at 1-800-FDA-1088.

How should I store EXXUA?

- Store EXXUA at room temperature between 68°F to 77°F (20°C to 25°C)
- Protect from high humidity and moisture.
- Keep EXXUA and all medicines out of the reach of children.

General information about the safe and effective use of EXXUA

Medicines are sometimes prescribed for purposes other than those listed in a Medication Guide.
Do not use EXXUA for a condition for which it was not prescribed. Do not give EXXUA to other people,
even if they have the same symptoms you have. It may harm them. You can ask your doctor or
pharmacist for information about EXXUA that is written for health professionals.

What are the ingredients in EXXUA?

Active ingredient:gepirone

Inactive ingredients:colloidal silicon dioxide, Hypromellose, iron oxide (red and/or yellow as
coloring agents), magnesium stearate, and microcrystalline cellulose.

This Medication Guide has been approved by the U.S. Food and Drug Administration. Issued 09/2023

Product of Italy

Manufactured by:

Mission Pharmacal Company

San Antonio, TX USA 78230

Distributed by:

Aytu Therapeutics, LLC

Denver, CO USA 80237

PRINCIPAL DISPLAY PANEL - 18.2 mg

NDC 23594-150-30

EXXUA 18.2 mg Tablets Bottles of 30 with child-resistant caps

PRINCIPAL DISPLAY PANEL - 36.3 MG

NDC 23594-151-30

EXXUA 36.3 mg Tablets Bottles of 30 with child-resistant caps

PRINCIPAL DISPLAY PANEL - 54.5 mg

NDC 23594-152-30

EXXUA 54.5 mg Tablets Bottles of 30 with child-resistant caps

PRINCIPAL DISPLAY PANEL - 72.6 mg

NDC 23594-153-30

EXXUA 72.6 mg Tablets Bottles of 30 with child-resistant caps